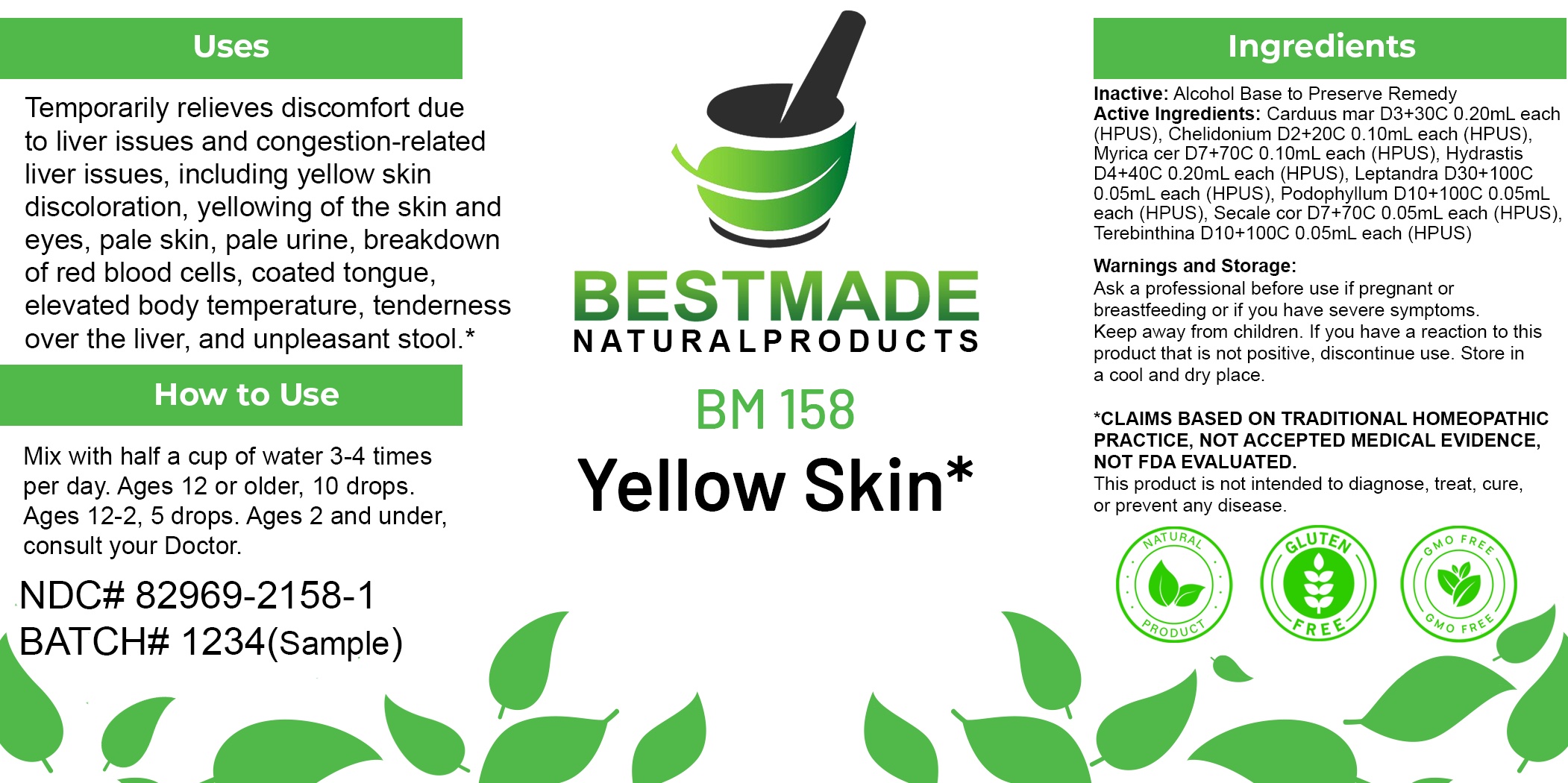 DRUG LABEL: Bestmade Natural Products BM158
NDC: 82969-2158 | Form: LIQUID
Manufacturer: Bestmade Natural Products
Category: homeopathic | Type: HUMAN OTC DRUG LABEL
Date: 20250218

ACTIVE INGREDIENTS: GOLDENSEAL 30 [hp_C]/30 [hp_C]; CLAVICEPS PURPUREA SCLEROTIUM 30 [hp_C]/30 [hp_C]; PODOPHYLLUM 30 [hp_C]/30 [hp_C]; CHELIDONIUM MAJUS WHOLE 30 [hp_C]/30 [hp_C]; TURPENTINE OIL 30 [hp_C]/30 [hp_C]; MILK THISTLE 30 [hp_C]/30 [hp_C]; VERONICASTRUM VIRGINICUM ROOT 30 [hp_C]/30 [hp_C]; MYRICA CERIFERA ROOT BARK 30 [hp_C]/30 [hp_C]
INACTIVE INGREDIENTS: ALCOHOL 30 [hp_C]/30 [hp_C]

BM158

ACTIVE INGREDIENTS:

Carduus mar D3+30C 0.20mL each (HPUS), Chelidonium D2+20C 0.10mL each (HPUS), Myrica cer D7+70C 0.10mL each (HPUS), Hydrastis D4+40C 0.20mL each (HPUS), Leptandra D30+100C 0.05mL each (HPUS), Podophyllum D10+100C 0.05mL each (HPUS), Secale cor D7+70C 0.05mL each (HPUS), Terebinthina D10+100C 0.05mL each (HPUS)

Inactive:

Alcohol Base to Preserve Product

DOSAGE AND ADMINISTRATION

How to Use

Mix with half a cup of water 3-4 times per day. Ages 12 or older, 10 drops. Ages 12-2, 5 drops. Ages 2 and under, consult your Doctor.

Uses
Temporarily relieves discomfort due to liver issues and congestion-related liver issues, including yellow skin discoloration, yellowing of the skin and eyes, pale skin, pale urine, breakdown of red blood cells, coated tongue, elevated body temperature, tenderness over the liver, and unpleasant stool.*

Uses
Temporarily relieves discomfort due to liver issues and congestion-related liver issues, including yellow skin discoloration, yellowing of the skin and eyes, pale skin, pale urine, breakdown of red blood cells, coated tongue, elevated body temperature, tenderness over the liver, and unpleasant stool.*

KEEP OUT OF REACH OF CHILDREN

Warnings and Storage:

Ask a professional before use if pregnant or breastfeeding or if you have severe symptoms.

Keep away from children. If you have a reaction to this product that is not positive, discontinue use. Store in a cool and dry place

*CLAIMS BASED ON TRADITIONAL HOMEOPATHIC PRACTICE, NOT ACCEPTED MEDICAL EVIDENCE NOT FDA EVALUATED.
This product is not intended to diagnose, treat, cure, or prevent any disease.

Warnings and Storage:

Ask a professional before use if pregnant or breastfeeding or if you have severe symptoms.

Keep away from children. If you have a reaction to this product that is not positive, discontinue use. Store in a cool and dry place

*CLAIMS BASED ON TRADITIONAL HOMEOPATHIC PRACTICE, NOT ACCEPTED MEDICAL EVIDENCE NOT FDA EVALUATED.
This product is not intended to diagnose, treat, cure, or prevent any disease.

Entire package label.